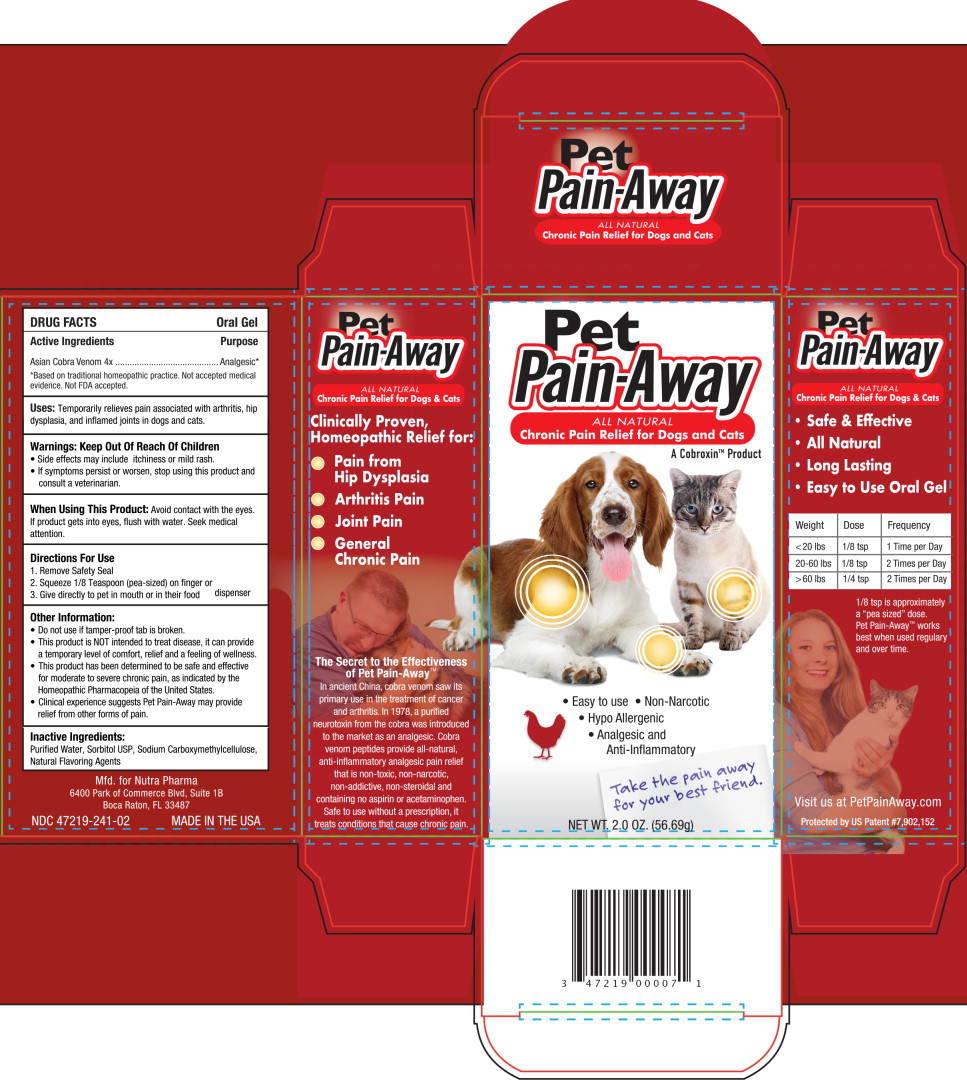 DRUG LABEL: Pet Pain Away
NDC: 47219-241 | Form: GEL
Manufacturer: Nutra Pharma Corporation
Category: homeopathic | Type: OTC ANIMAL DRUG LABEL
Date: 20250916

ACTIVE INGREDIENTS: NAJA NAJA VENOM 70 ug/1 mL
INACTIVE INGREDIENTS: WATER; SORBITOL; CARBOXYMETHYLCELLULOSE SODIUM, UNSPECIFIED

DRUG FACTS Oral Gel

Active Ingredients

Asian Cobra Venom 4x

Purpose

Analgesic*

*Based on traditional homeopathic practice. Not accepted medical evidence. Not FDA accepted.

Uses:

Temporarily relieves pain associated with arthritis, hip dysplasia, and inflamed joints in dogs and cats.

Warnings:

Keep Out Of Reach Of Children

- Side effects may include itchiness or mild rash.
- If symptoms persist or worsen, stop using this product and consult a veterinarian.

When Using This Product:

Avoid contact with the eyes. If product gets into eyes, flush with water. Seek medical attention.

Directions For Use

1. Remove Safety Seal
2. Squeeze 1/8 Teaspoon (pea-sized) on finger or
3. Give directly to pet in mouth or in their food dispenser

Other Information:

- Do not use if tamper-proof tab is broken.
- This product is NOT intended to treat disease, it can provide a temporary level of comfort, relief and a feeling of wellness.
- This product has been determined to be safe and effective for moderate to severe chronic pain, as indicated by the Homeopathic Pharmacopeia of the United States.
- Clinical experience suggests Pet Pain-Away may provide relief from other forms of pain.

Inactive Ingredients:

Purified Water, Sorbitol USP, Sodium Carboxymethylcellulose, Natural Flavoring Agents

Mfd. for Nutra Pharma 6400 Park of Commerce Blvd, Suite 1B Boca Raton, FL 33487

NDC 47219-241 -02 MADE IN THE USA

Principal Display Panel - 56.69 g Carton Label

Pet
Pain Away

ALL NATURAL
Chronic Pain Relief for Dogs and Cats
A Cobroxin™ Product

• Easy to use • Non-Narcotic
• Hypo Allergenic
• Analgesic and
Anti-Inflammatory

Take the pain away
for your best friend.

NET WT. 2.0 OZ. (56.69g)